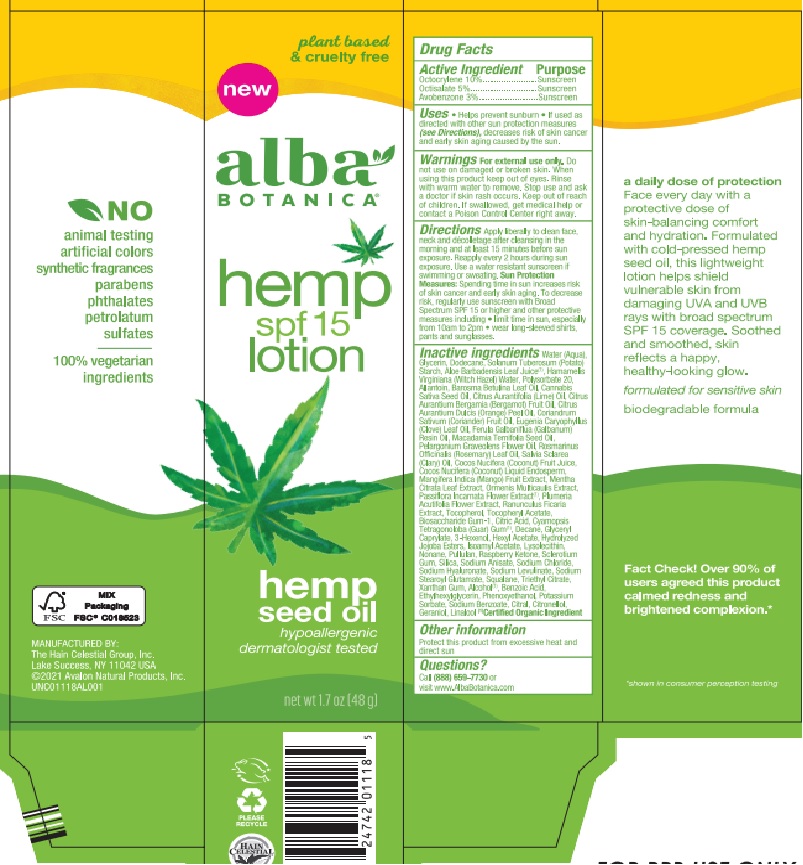 DRUG LABEL: Alba Hemp SPF15
NDC: 61995-3036 | Form: LOTION
Manufacturer: The Hain Celestial Group
Category: otc | Type: HUMAN OTC DRUG LABEL
Date: 20231205

ACTIVE INGREDIENTS: OCTISALATE 5 g/100 g; AVOBENZONE 3 g/100 g; OCTOCRYLENE 10 g/100 g
INACTIVE INGREDIENTS: TRIETHYL CITRATE; .BETA.-CITRONELLOL, (+/-)-; BIOSACCHARIDE GUM-1; GUAR GUM; STARCH, POTATO; ANHYDROUS CITRIC ACID; VERONICA OFFICINALIS FLOWERING TOP; WATER; COCONUT ALKANES; GLYCERIN; ALOE VERA LEAF; ALCOHOL; PHENOXYETHANOL; POTASSIUM SORBATE; SODIUM BENZOATE; CITRAL; LINALOOL, (+/-)-; .ALPHA.-TOCOPHEROL ACETATE, DL-; PASSIFLORA INCARNATA FLOWER; ORANGE PEEL; CLARY SAGE OIL; MACADAMIA TERNIFOLIA WHOLE; 3-HEXANOL; 4-(AMINOMETHYL)BENZOIC ACID HYDROCHLORIDE; LIME OIL; HYDRATED SILICA; SQUALANE; 1,12-DI(3-DECYL-2-METHYLIMIDAZOLIUM)DODECANE DIBROMIDE; WITCH HAZEL; BERGAMOT OIL; GUM TALHA; HYDROLYZED JOJOBA ESTERS (ACID FORM); MANGO JUICE; HEXYL ACETATE; XANTHAN GUM; ETHYLHEXYLGLYCERIN; SODIUM ANISATE; AGATHOSMA BETULINA LEAF OIL; CLOVE LEAF OIL; ISOAMYL ACETATE; PELARGONIUM GRAVEOLENS FLOWER OIL; PULLULAN; ALLANTOIN PABA; CANNABIS SATIVA SEED OIL; CORIANDER OIL; ROSEMARY OIL; COCONUT OIL; ALPHA-TOCOPHEROL; NONANE; PEG-9 DIGLYCIDYL ETHER/SODIUM HYALURONATE CROSSPOLYMER; SODIUM LEVULINATE; GLYCERYL CAPRATE; POLYSORBATE 20; GALBANUM OIL; MENTHA CITRATA LEAF; CHAMOMILE FLOWER OIL; RANUNCULUS FICARIA WHOLE; DODECANE; LYSOBACTIN; GERANIOL; RASPBERRY JUICE; SODIUM CHLORIDE; SODIUM STEAROYL GLUTAMATE

AL01118 Alba Hemp SPF 15
156-045A-3

ACTIVE INGREDIENT

Avobenzone 3%

Octisalate 5%

Octocrylene 10%

DOSAGE AND ADMINISTRATION

Apply liberally 15 minutes before sun exposure. Reapply every 2 hours during sun exposure. Use water resistant sunscreen if swimming or sweating. Sun Protection Measures: Spending time in the sun increase risk of skin cancer and early skin aging. To decrease risk, regularly use sunscreen with Broad Spectrum SPF 15 or higherand other preventive measures including:

- Limit time in the sun, especially from 10am to 2pm
- wear long-sleeved shirts, pants and sunglasses

PURPOSE

Sunscreen

WARNINGS

For external use only. Do not use on damaged or broken skin. When using this product, keep out of eyes. Rinse with water to remove. Stop use and ask a doctor if skin rash occurs. If swallowed, get medical help or contact a Poison Control Center right away.

Keep out of reach of children.

INACTIVE INGREDIENT

Water (Aqua), Glycerin, Dodecane, Solanum Tuberosum (Potato) Starch, Aloe Barbadensis Leaf Juice (1), Hamamelis Virginiana (Witch Hazel) Water, Polysorbate 20, Allantoin, Barosma Betulina Leaf Oil, Cannabis Sativa Seed Oil, Citrus Aurantifolia (Lime) Oil, Citrus Aurantium Bergamia (Bergamot) Fruit Oil, Citrus Aurantium Dulcis (Orange) Peel Oil, Coriandrum Sativum (Coriander) Fruit Oil, Eugenia Caryophyllus (Clove) Leaf Oil, Ferula Galbaniflua (Galbanum) Resin Oil, Macadamia Ternifolia Seed Oil, Pelargonium Graveolens Flower Oil, Rosmarinus Officinalis (Rosemary) Leaf Oil, Salvia Sclarea (Clary) Oil, Cocos Nucifera (Coconut) Fruit Juice, Cocos Nucifera (Coconut) Liquid Endosperm, Mangifera Indica (Mango) Fruit Extract, Mentha Citrata Leaf Extract, Ormenis Multicaulis Extract, Passiflora Incarnata Flower Extract (1), Plumeria Acutifolia Flower Extract, Ranunculus Ficaria Extract, Tocopherol, Tocopheryl Acetate, Biosaccharide Gum-1, Citric Acid, Cyamopsis Tetragonoloba (Guar) Gum (1), Decane, Glyceryl Caprylate, 3-Hexenol, Hexyl Acetate, Hydrolyzed Jojoba Esters, Isoamyl Acetate, Lysolecithin, Nonane, Pullulan, Raspberry Ketone, Sclerotium Gum, Silica, Sodium Anisate, Sodium Chloride, Sodium Hyaluronate, Sodium Levulinate, Sodium Stearoyl Glutamate, Squalane, Triethyl Citrate, Xanthan Gum, Alcohol (1), Benzoic Acid, Ethylhexylglycerin, Phenoxyethanol, Potassium Sorbate, Sodium Benzoate, Citral, Citronellol, Geraniol, Linalool.

(1) Certified Organic Ingredient

INDICATIONS AND USAGE

Sunscreen